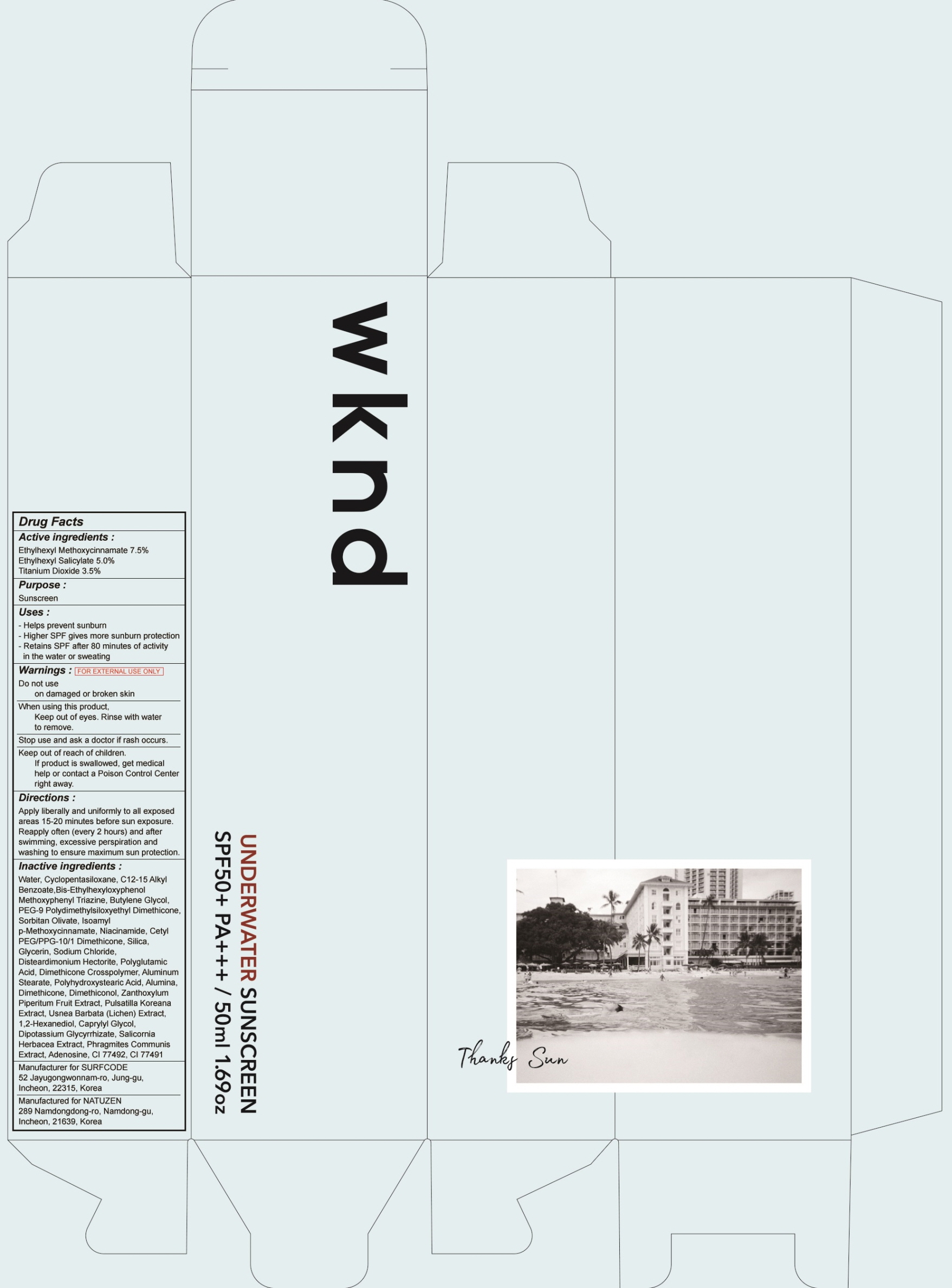 DRUG LABEL: WKND UNDERWATER SUN SCREEN
NDC: 71192-050 | Form: CREAM
Manufacturer: SURFCODE
Category: otc | Type: HUMAN OTC DRUG LABEL
Date: 20191223

ACTIVE INGREDIENTS: OCTINOXATE 3.75 g/50 mL; OCTISALATE 2.5 g/50 mL; TITANIUM DIOXIDE 1.75 g/50 mL
INACTIVE INGREDIENTS: Butylene Glycol; Sorbitan Olivate

ACTIVE INGREDIENT

Active Ingredient: ETHYLHEXYL METHOXYCINNAMATE 7.50%, ETHYLHEXYL SALICYLATE 5.00%, TITANIUM DIOXIDE 3.5%

INACTIVE INGREDIENT

Inactive Ingredients:

Water, Cyclopentasiloxane, C12-15 Alkyl Benzoate, Bis-Ethylhexyloxyphenol Methoxyphenyl Triazine, Butylene Glycol, PEG-9 Polydimethylsiloxyethyl Dimethicone, Sorbitan Olivate, Isoamyl p-Methoxycinnamate, Niacinamide, Cetyl PEG/PPG-10/1 Dimethicone, Silica, Glycerin, Sodium Chloride, Disteardimonium Hectorite, Polyglutamic Acid, Dimethicone Crosspolymer, Aluminum Stearate, Polyhydroxystearic Acid, Alumina, Dimethicone, Dimethiconol, Zanthoxylum Piperitum Fruit Extract, Pulsatilla Koreana Extract, Usnea Barbata (Lichen) Extract, 1,2-Hexanediol, Caprylyl Glycol, Dipotassium Glycyrrhizate, Salicornia Herbacea Extract, Phragmites Communis Extract, Adenosine, CI 77492, CI 77491

PURPOSE

Purpose: Sunscreen

WARNINGS

FOR EXTERNAL USE ONLY

- Do not use on damaged or broken skin

- When using this product, Keep out of eyes. Rinse with water to remove.

- Stop use and ask a doctor if rash occurs.

- Keep out of reach of children. If product is swallowed, get medical help or contact a Poison Control Center right away.

DESCRIPTION

Direction: - Apply liberally and uniformly to all exposed areas 15-20 minutes before sun exposure. Reapply often (every 2 hours) and after swimming, excessive perspiration and washing to ensure maximum sun protection.

Uses: - Helps prevent sunburn - Higher SPF gives more sunburn protection - Retains SPF after 80 minutes of activity in the water or sweating